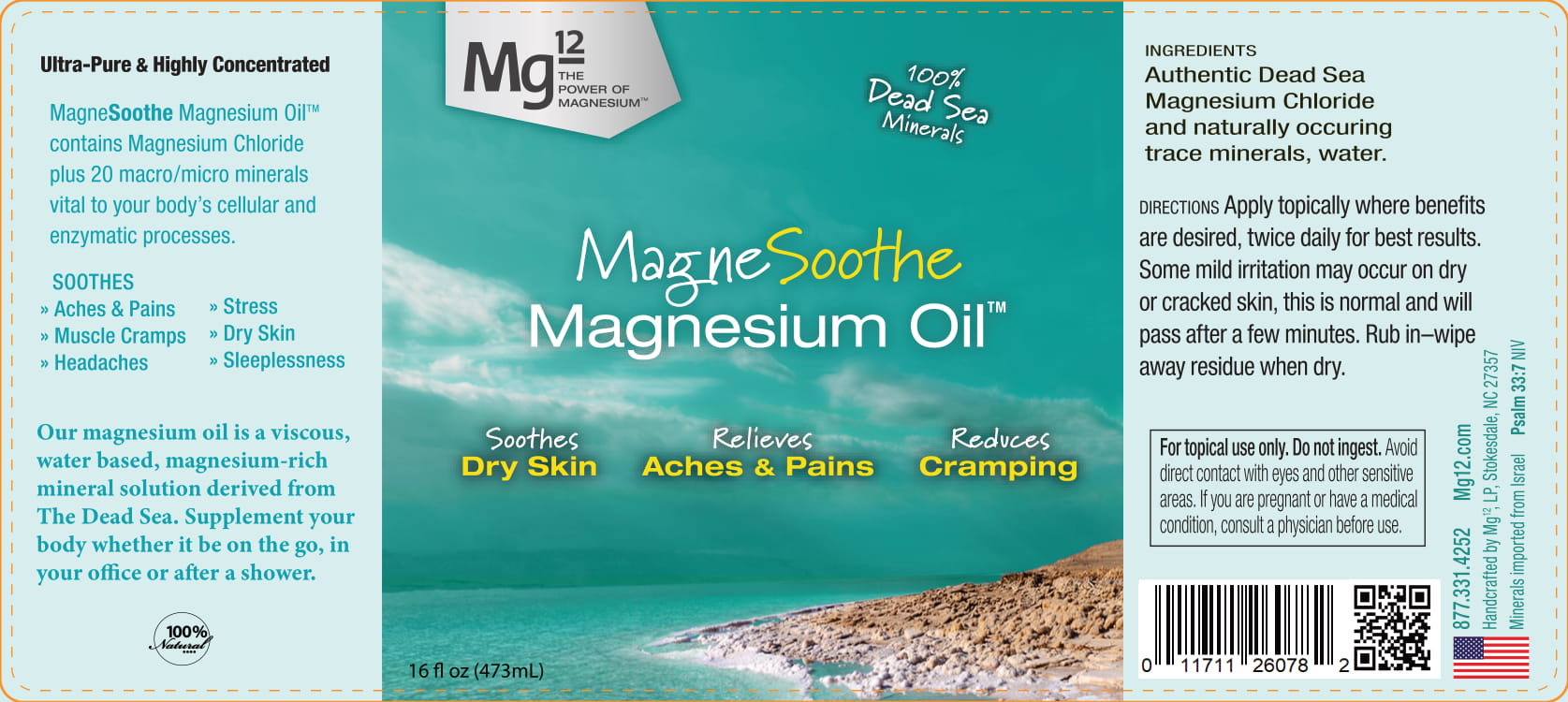 DRUG LABEL: Magnesoothe Magnesium Oil
NDC: 78735-1000 | Form: LIQUID
Manufacturer: Mg12, LP
Category: otc | Type: HUMAN OTC DRUG LABEL
Date: 20201018

ACTIVE INGREDIENTS: ISOPROPYL ALCOHOL 10 g/100 g
INACTIVE INGREDIENTS: MAGNESIUM CHLORIDE 60 g/100 g; WATER 30 g/100 g

Magnesoothe Magnesium Oil

Purpose

The purpose of this product is to reduce pain.

How to Apply

Rub 5 ml of product (one pump) thoroughly into epidermis.

Dosage

7.5 grams (or .075ml) grams of magnesium per pump.

Ingredients

No active Ingredients

Ingredients

60 ml Magnesium Chloride per 100 ml

40 ml Water per 100 ml

Warnings

Information on toxicological effects
Skin corrosion/irritation
Not applicible
Serious eye damage/irritation
Causes eye irritation.
Respiratory or skin sensitization
May cause an allergic skin reaction
Germ cell mutagenicity
Not applicible

Carcinogenicity
ACGIH: No component of this product present at levels greater than or equal to 0.1% is identified as a
carcinogen or potential carcinogen by ACGIH.
Reproductive toxicity
Not applicible
STOT-single exposure
Not applicible
STOT-repeated exposure
Not applicible
Aspiration hazard
May be harmful if swallowed and enters airways

_____________ More Infromation _____________

Canadian Domestic Substances List (DSL)
Chemical name: Magnesium chloride (MgCl2)
CAS: 7786-30-3
SARA 302 Components
No chemicals in this material are subject to the reporting requirements of SARA Title III, Section 302.
SARA 313 Components
This material does not contain any chemical components with known CAS numbers that exceed the
threshold (De Minimis) reporting levels established by SARA Title III, Section 313.
SARA 311/312 Hazards
No SARA Hazards
Massachusetts Right To Know Components
No components are subject to the Massachusetts Right to Know Act.

Pennsylvania Right To Know Components
Water
CAS-No. 7732-18-5
New Jersey Right To Know Components
Water
CAS-No. 7732-18-5
California Prop. 65 Components
This product does not contain any chemicals known to State of California to cause cancer, birth defects, or
any other reproductive harm.
Canadian Domestic Substances List (DSL)
Chemical name: Water
CAS: 7732-18-5

Keep Out of Reach of Children

See warnings section

PACKAGE LABEL

118 ml per bottle 78735-1000-4